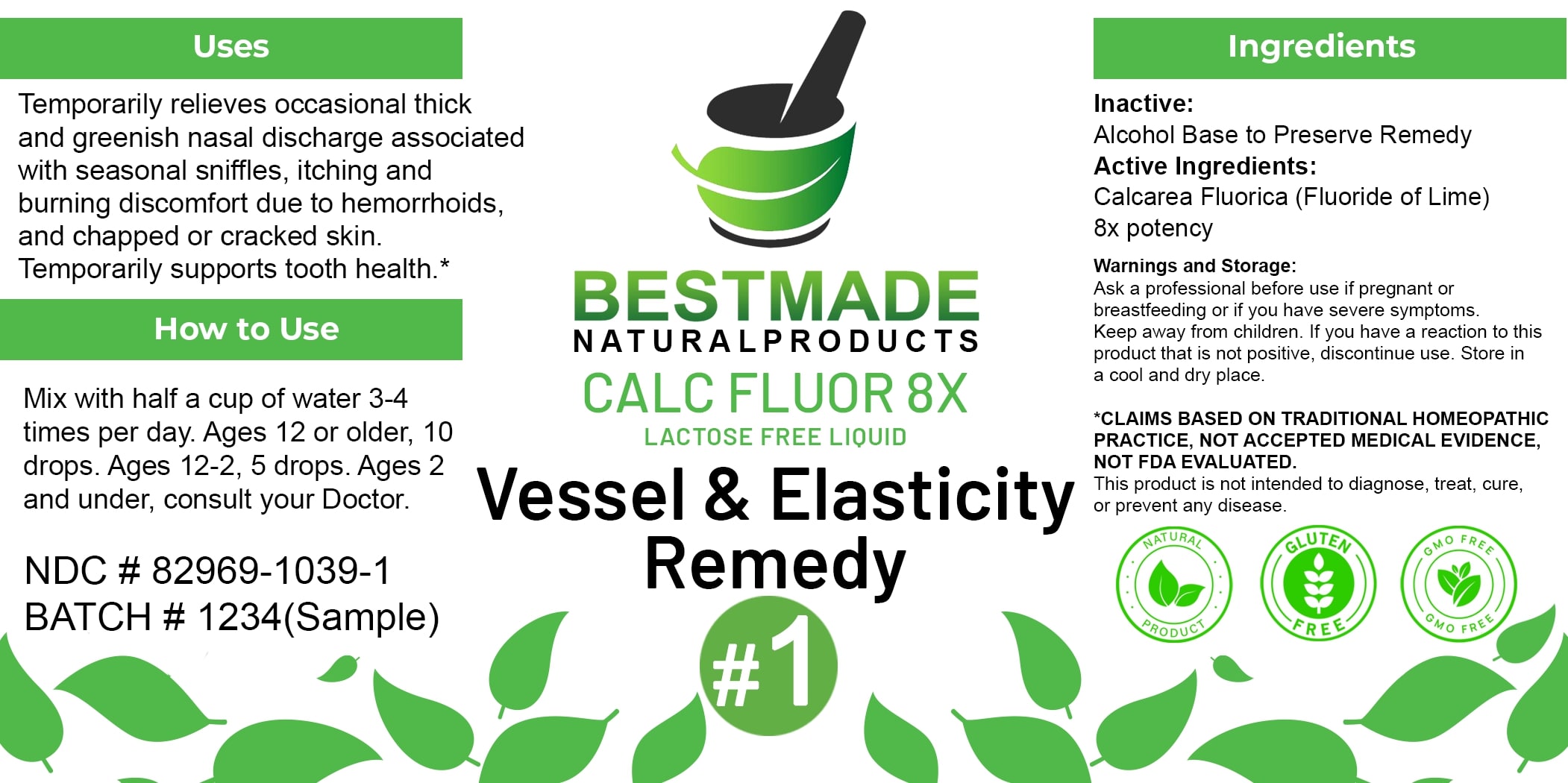 DRUG LABEL: Bestmade Natural Products Calc Fluor 8x
NDC: 82969-1039 | Form: LIQUID
Manufacturer: Bestmade Natural Products
Category: homeopathic | Type: HUMAN OTC DRUG LABEL
Date: 20250403

ACTIVE INGREDIENTS: CALCIUM FLUORIDE 8 [hp_X]/8 [hp_X]
INACTIVE INGREDIENTS: ALCOHOL 8 [hp_X]/8 [hp_X]

Calc Fluor 8x - liquid lactose free

DOSAGE AND ADMINISTRATION

How to Use

Mix with half a cup of water 3-4 times per day. Ages 12 or older, 10 drops. Ages 12-2, 5 drops. Ages 2 and under, consult your Doctor.

Uses

Temporarily relieves occasional thick and greenish nasal discharge associated with seasonal sniffles, itching and burning discomfort due to hemorrhoids and chapped or cracked skin. Temporarily supports tooth health.*

*CLAIMS BASED ON TRADITIONAL HOMEOPATHIC PRACTICE, NOT ACCEPTED MEDICAL EVIDENCE. NOT FDA EVALUATED.

This product is not intended to diagnose, treat, cure, or prevent any disease.

Inactive:
Alcohol Base to Preserve Remedy

Active Ingredients:
Calcarea Fluorica (Fluoride of Lime) 8x potency

KEEP OUT OF REACH OF CHILDREN

Warnings and Storage:

Ask a professional before use if pregnant or breastfeeding or if you have severe symptoms. Keep away from children. If you have a reaction to this product that is not positive, discontinue use. Store in a cool and dry place.

Uses

Temporarily relieves occasional thick and greenish nasal discharge associated with seasonal sniffles, itching and burning discomfort due to hemorrhoids and chapped or cracked skin. Temporarily supports tooth health.*

*CLAIMS BASED ON TRADITIONAL HOMEOPATHIC PRACTICE, NOT ACCEPTED MEDICAL EVIDENCE. NOT FDA EVALUATED.

This product is not intended to diagnose, treat, cure, or prevent any disease.

Warnings and Storage:

Ask a professional before use if pregnant or breastfeeding or if you have severe symptoms. Keep away from children. If you have a reaction to this product that is not positive, discontinue use. Store in a cool and dry place.

*CLAIMS BASED ON TRADITIONAL HOMEOPATHIC PRACTICE, NOT ACCEPTED MEDICAL EVIDENCE. NOT FDA EVALUATED.

This product is not intended to diagnose, treat, cure, or prevent any disease.

Entire package label